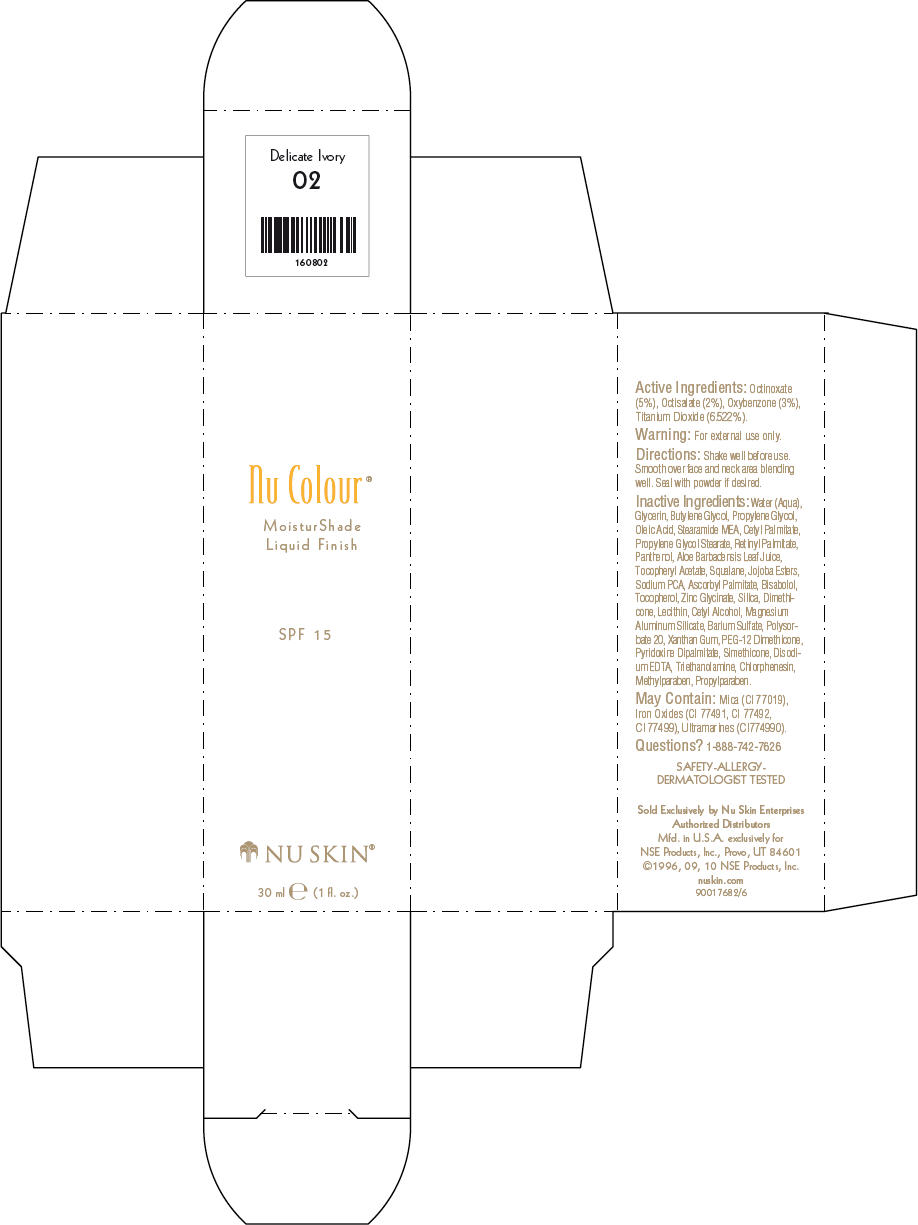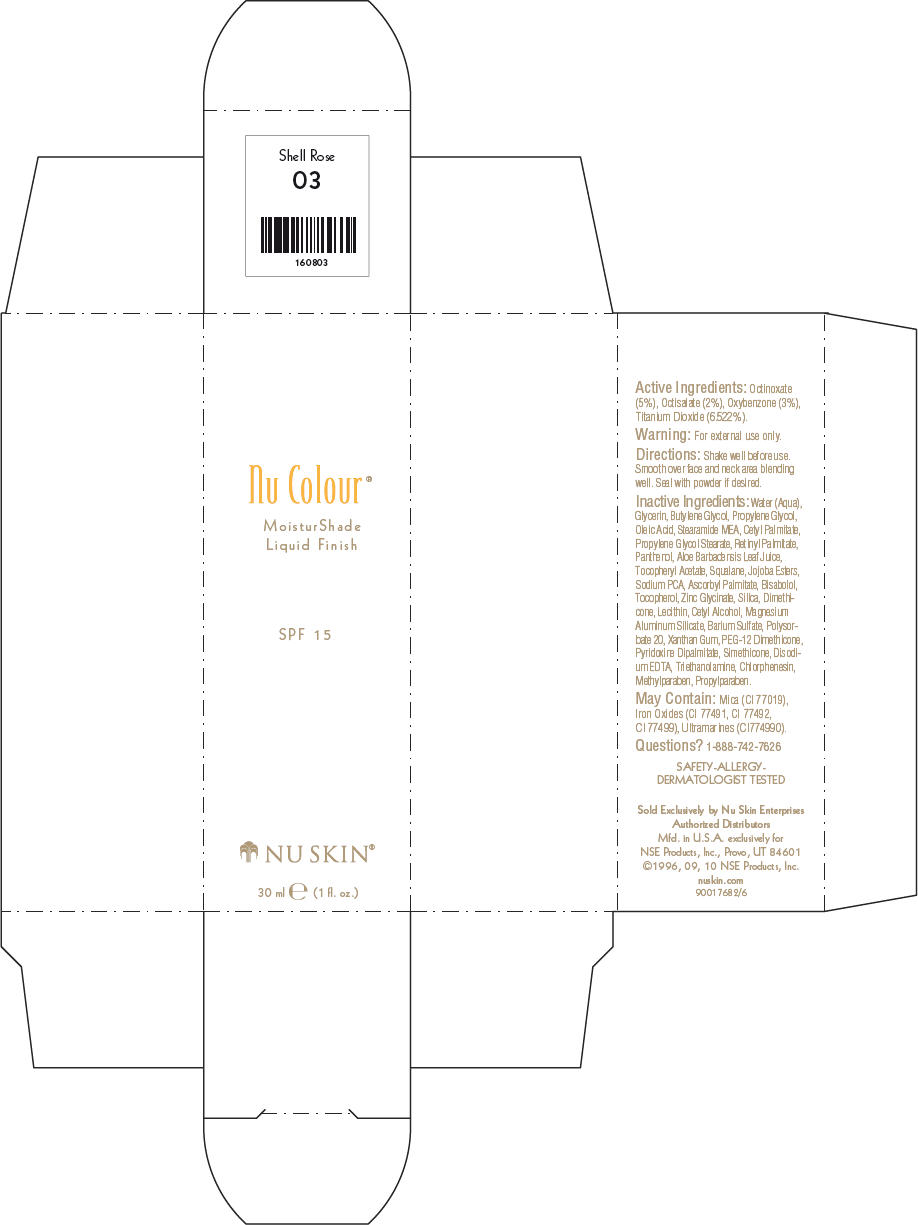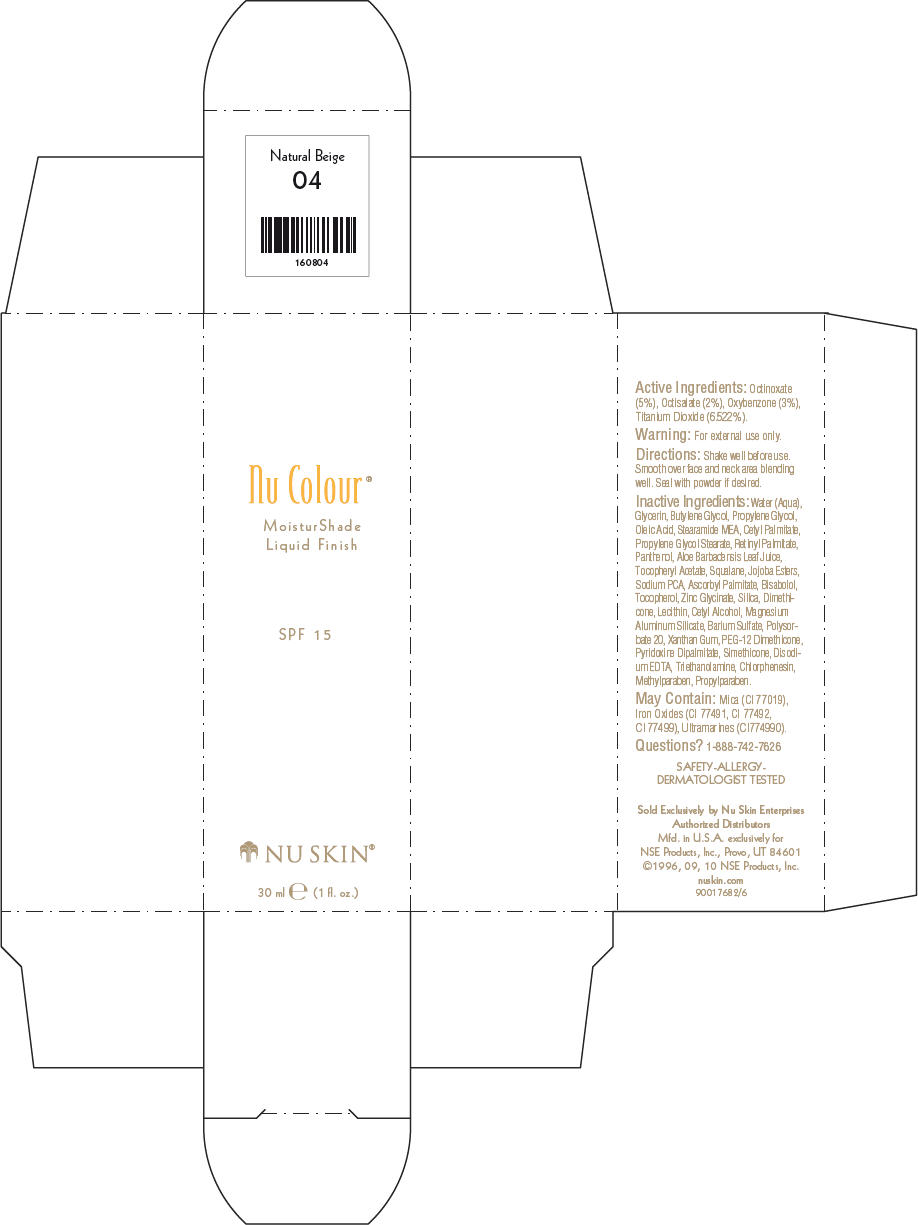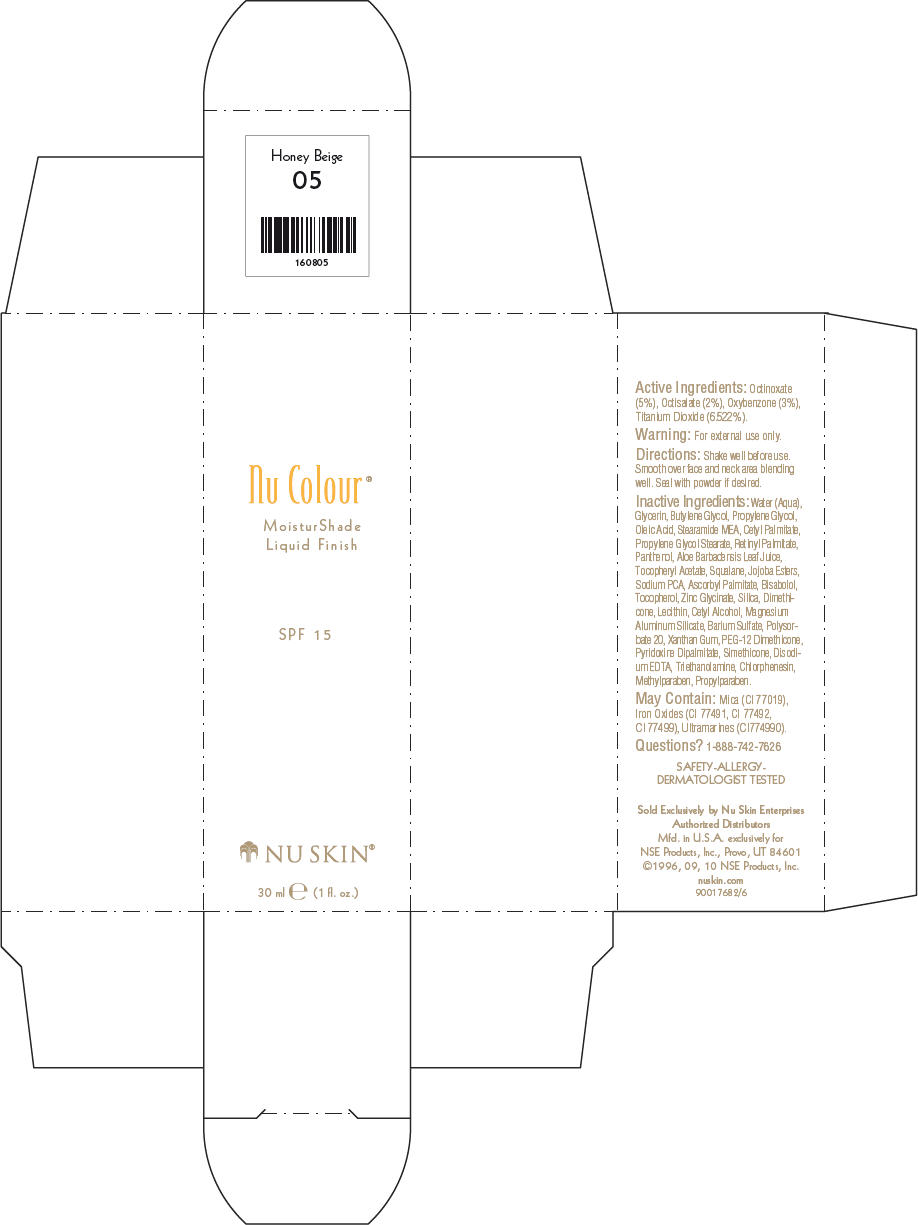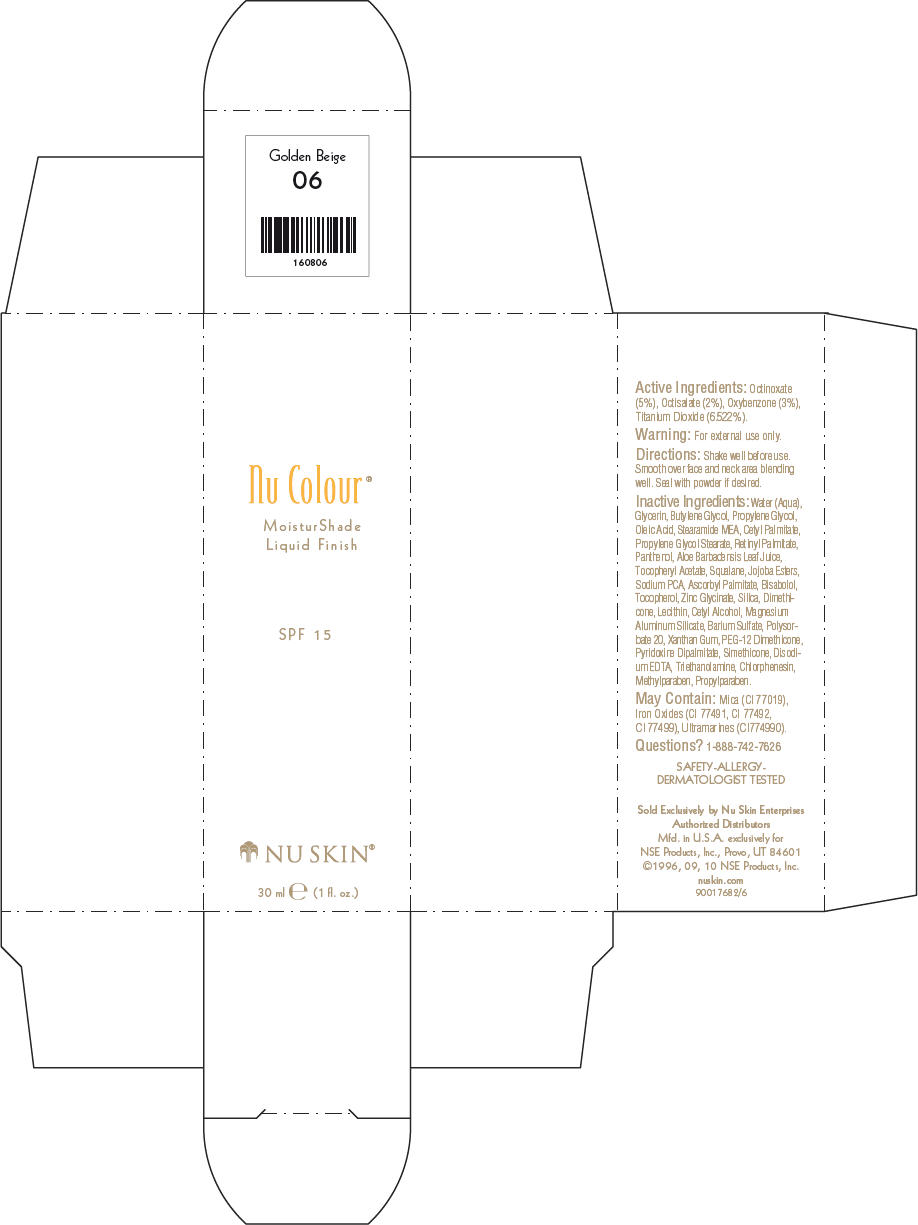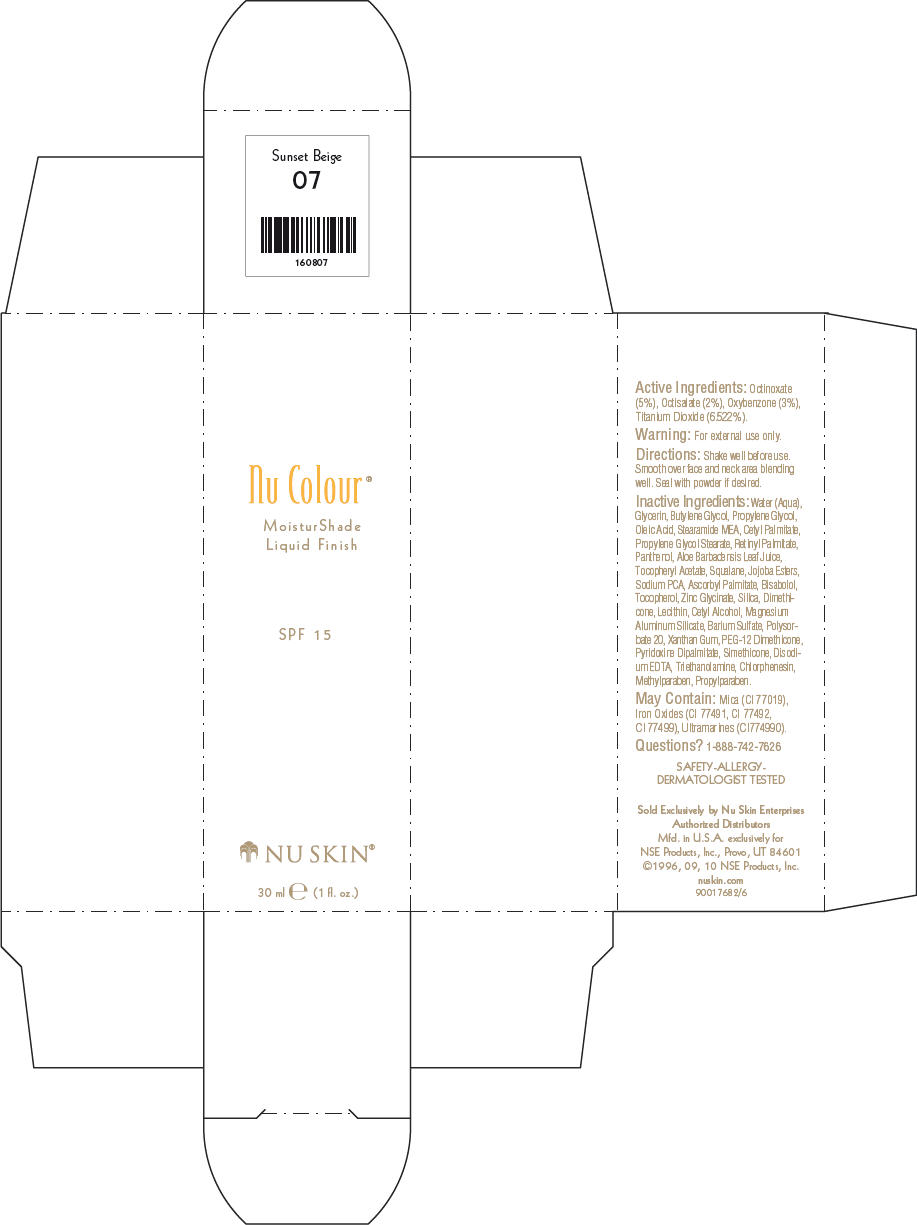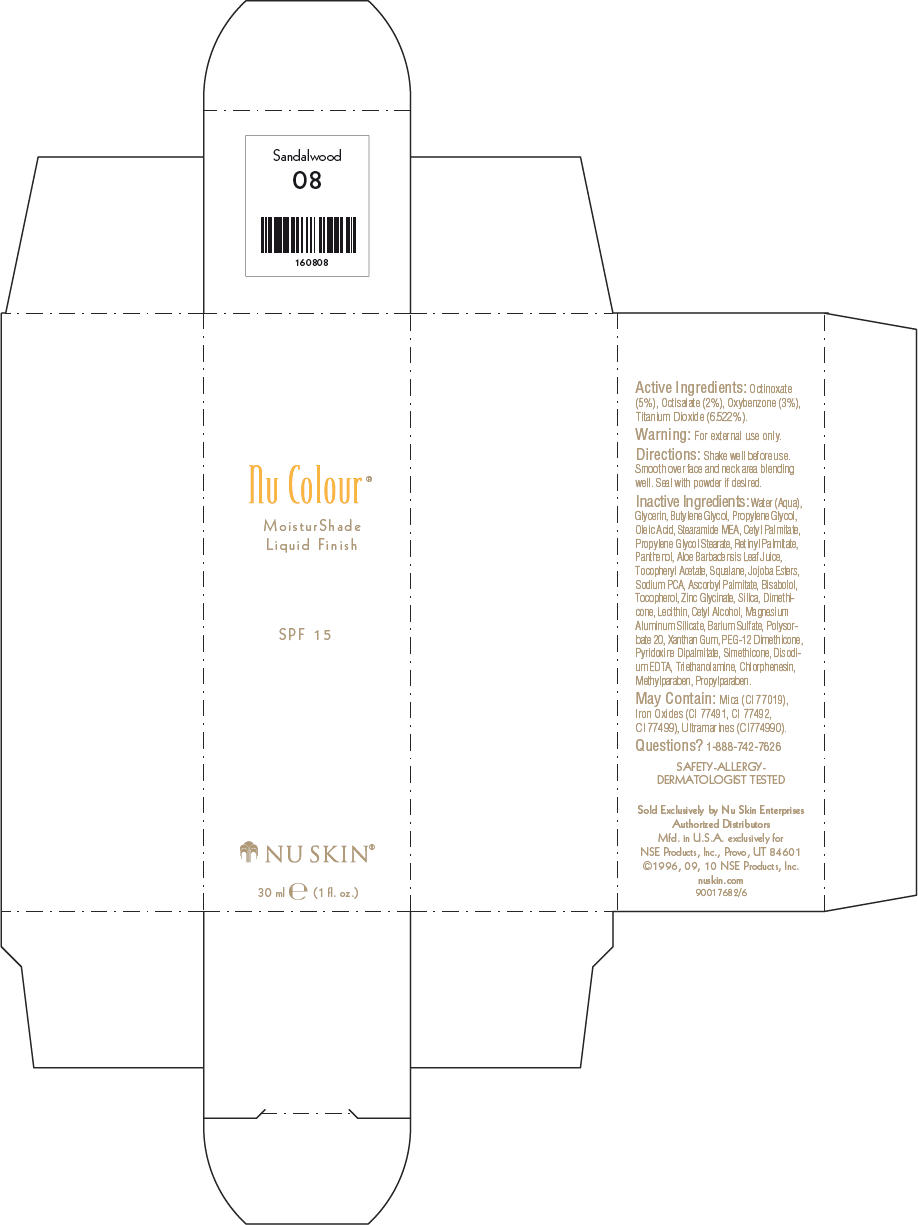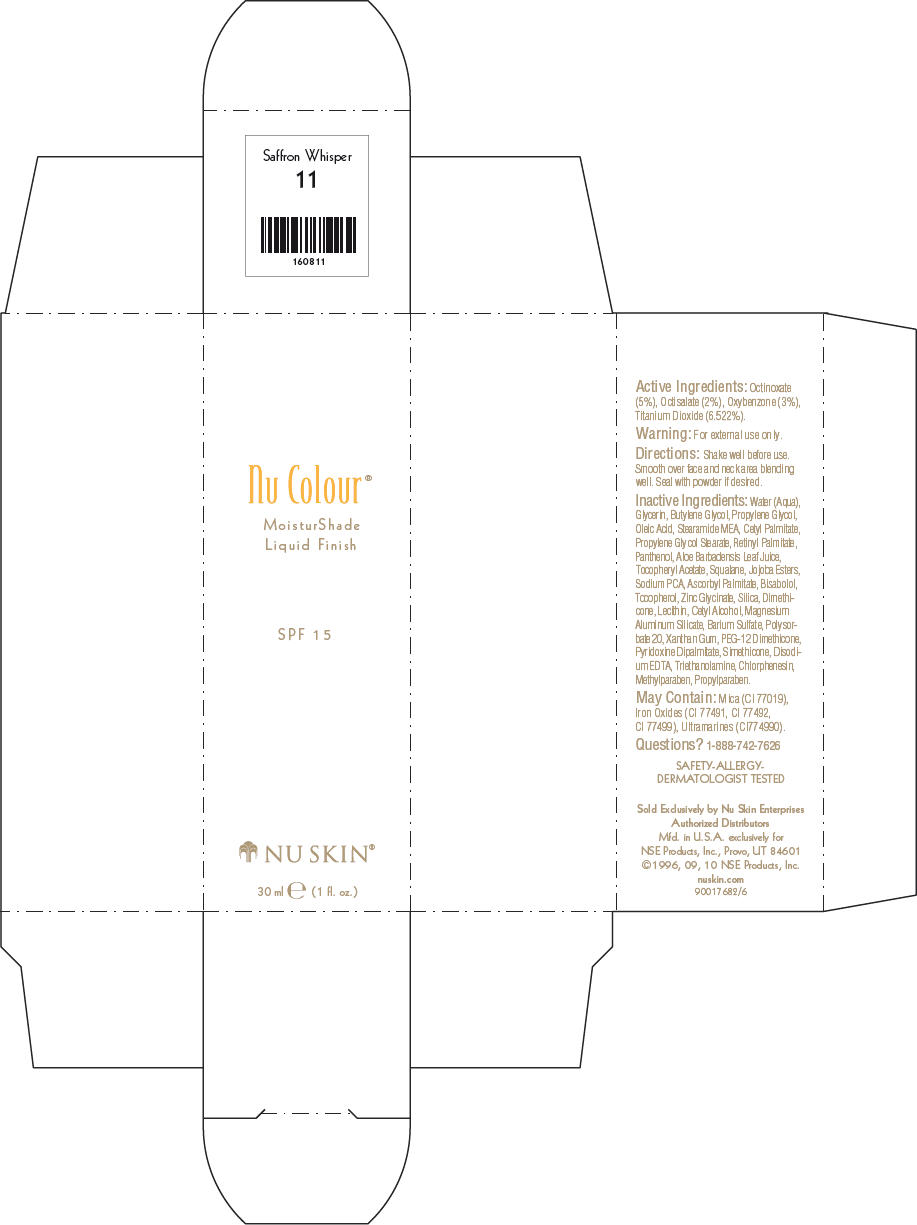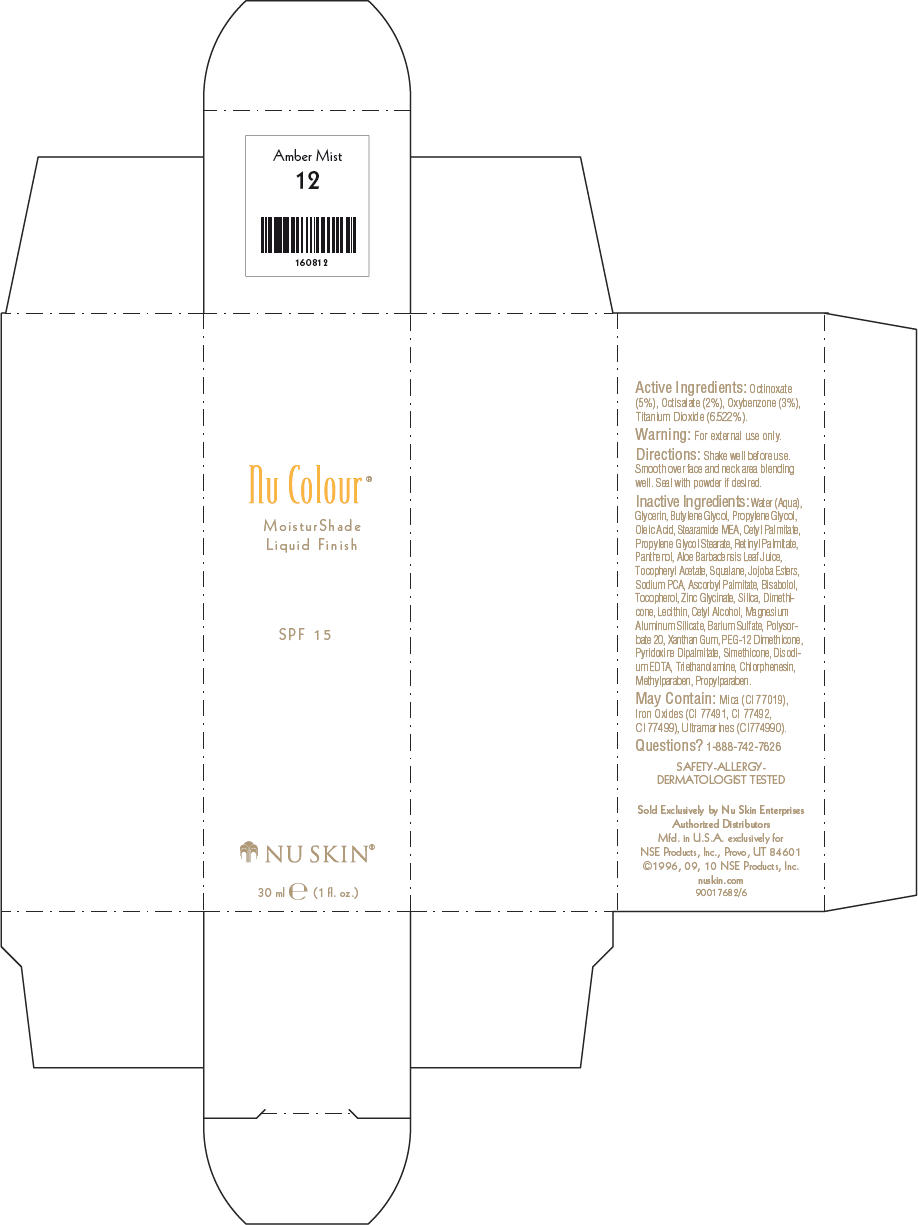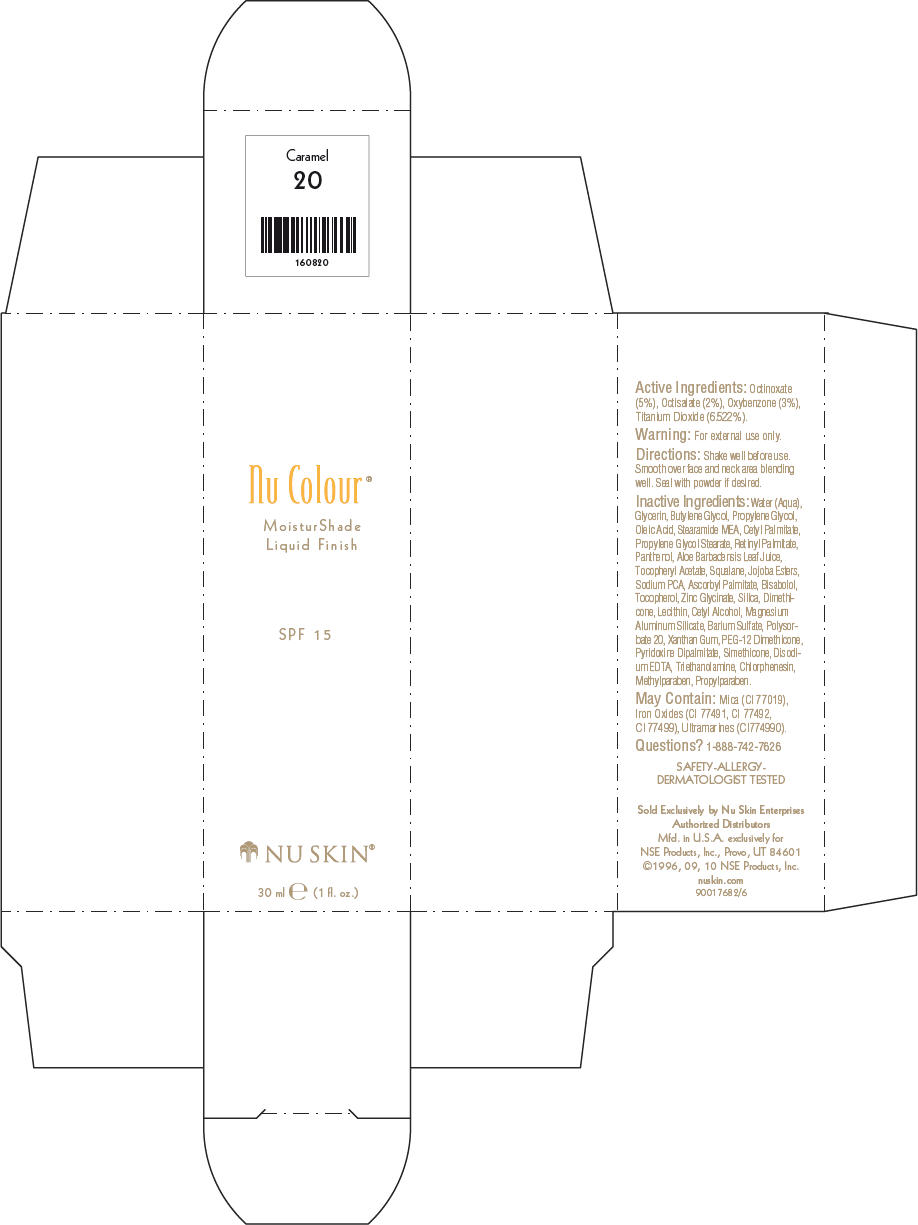 DRUG LABEL: Nu Skin Nu Colour 
NDC: 62839-0802 | Form: LOTION
Manufacturer: NSE Products, Inc.
Category: otc | Type: HUMAN OTC DRUG LABEL
Date: 20110603

ACTIVE INGREDIENTS: Octinoxate 50 g/1000 mL; Octisalate 20 g/1000 mL; Oxybenzone 30 g/1000 mL; Titanium Dioxide 65.22 g/1000 mL
INACTIVE INGREDIENTS: Water; Glycerin; Butylene Glycol; Propylene Glycol; Oleic Acid; Stearic Monoethanolamide; Cetyl Palmitate; Propylene Glycol Monostearate; Vitamin A Palmitate; Panthenol; Aloe Vera Leaf; Squalene; Sodium Pyrrolidone Carboxylate; Ascorbyl Palmitate; Levomenol; Tocopherol; Silicon Dioxide; Dimethicone; Cetyl Alcohol; Magnesium Aluminum Silicate; Barium Sulfate; Polysorbate 20; Xanthan Gum; PEG-12 Dimethicone; Edetate Disodium; Trolamine; Chlorphenesin; Methylparaben; Propylparaben; Mica; FERRIC OXIDE RED; FERRIC OXIDE YELLOW; FERROSOFERRIC OXIDE

Nu Colour®
MoisturShade
Liquid Finish

Active Ingredients

Octinoxate (5%), Octisalate (2%), Oxybenzone (3%), Titanium Dioxide (6.522%).

Warning

For external use only.

Directions

Shake well before use. Smooth over face and neck area blending well. Seal with powder if desired.

Inactive Ingredients

Water (Aqua), Glycerin, Butylene Glycol, Propylene Glycol, Oleic Acid, Stearamide MEA, Cetyl Palmitate, Propylene Glycol Stearate, Retinyl Palmitate, Panthenol, Aloe Barbadensis Leaf Juice, Tocopheryl Acetate, Squalane, Jojoba Esters, Sodium PCA, Ascorbyl Palmitate, Bisabolol, Tocopherol, Zinc Glycinate, Silica, Dimethicone, Lecithin, Cetyl Alcohol, Magnesium Aluminum Silicate, Barium Sulfate, Polysorbate 20, Xanthan Gum, PEG-12 Dimethicone, Pyridoxine Dipalmitate, Simethicone, Disodium EDTA, Triethanolamine, Chlorphenesin, Methylparaben, Propylparaben.

May Contain

Mica (CI 77019), Iron Oxides (CI 77491, CI 77492, CI 77499), Ultramarines (CI774990).

Questions?

1-888-742-7626

PRINCIPAL DISPLAY PANEL - 30 ml Delicate Ivory Carton

Nu Colour®

MoisturShade
Liquid Finish

SPF 15

NU SKIN®

30 ml e (1 fl. oz.)

PRINCIPAL DISPLAY PANEL - 30 ml Shell Rose Carton

Nu Colour®

MoisturShade
Liquid Finish

SPF 15

NU SKIN®

30 ml e (1 fl. oz.)

PRINCIPAL DISPLAY PANEL - 30 ml Natural Beige Carton

Nu Colour®

MoisturShade
Liquid Finish

SPF 15

NU SKIN®

30 ml e (1 fl. oz.)

PRINCIPAL DISPLAY PANEL - 30 ml Honey Beige Carton

Nu Colour®

MoisturShade
Liquid Finish

SPF 15

NU SKIN®

30 ml e (1 fl. oz.)

PRINCIPAL DISPLAY PANEL - 30 ml Golden Beige Carton

Nu Colour®

MoisturShade
Liquid Finish

SPF 15

NU SKIN®

30 ml e (1 fl. oz.)

PRINCIPAL DISPLAY PANEL - 30 ml Sunset Beige Carton

Nu Colour®

MoisturShade
Liquid Finish

SPF 15

NU SKIN®

30 ml e (1 fl. oz.)

PRINCIPAL DISPLAY PANEL - 30 ml Sandalwood Carton

Nu Colour®

MoisturShade
Liquid Finish

SPF 15

NU SKIN®

30 ml e (1 fl. oz.)

PRINCIPAL DISPLAY PANEL - 30 ml Saffron Whisper Carton

Nu Colour®

MoisturShade
Liquid Finish

SPF 15

NU SKIN®

30 ml e (1 fl. oz.)

PRINCIPAL DISPLAY PANEL - 30 ml Amber Mist Carton

Nu Colour®

MoisturShade
Liquid Finish

SPF 15

NU SKIN®

30 ml e (1 fl. oz.)

PRINCIPAL DISPLAY PANEL - 30 ml Caramel Carton

Nu Colour®

MoisturShade
Liquid Finish

SPF 15

NU SKIN®

30 ml e (1 fl. oz.)